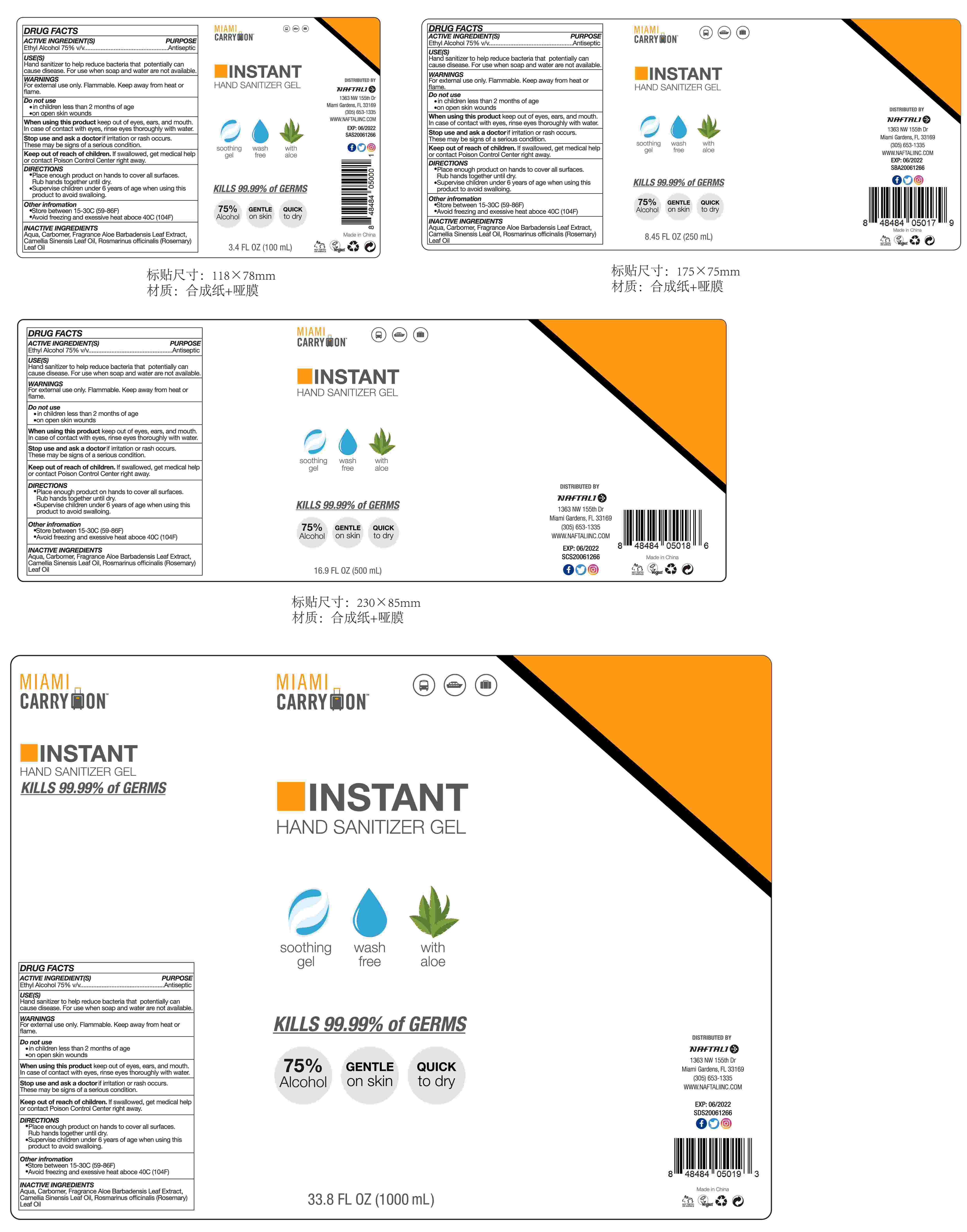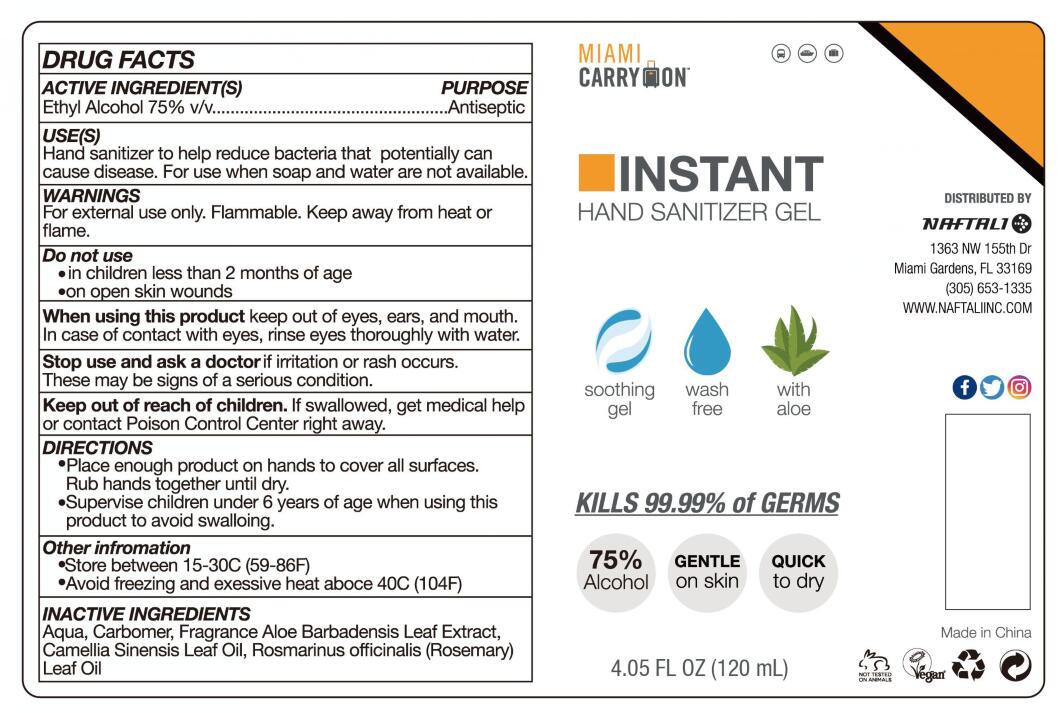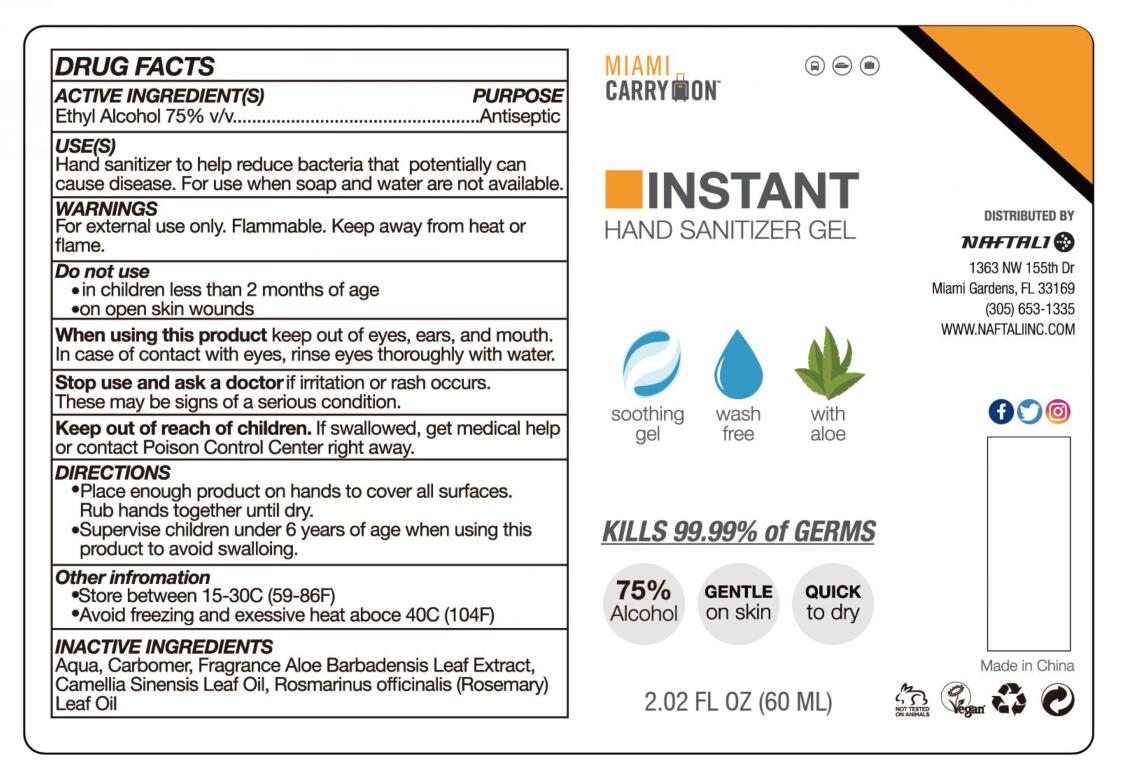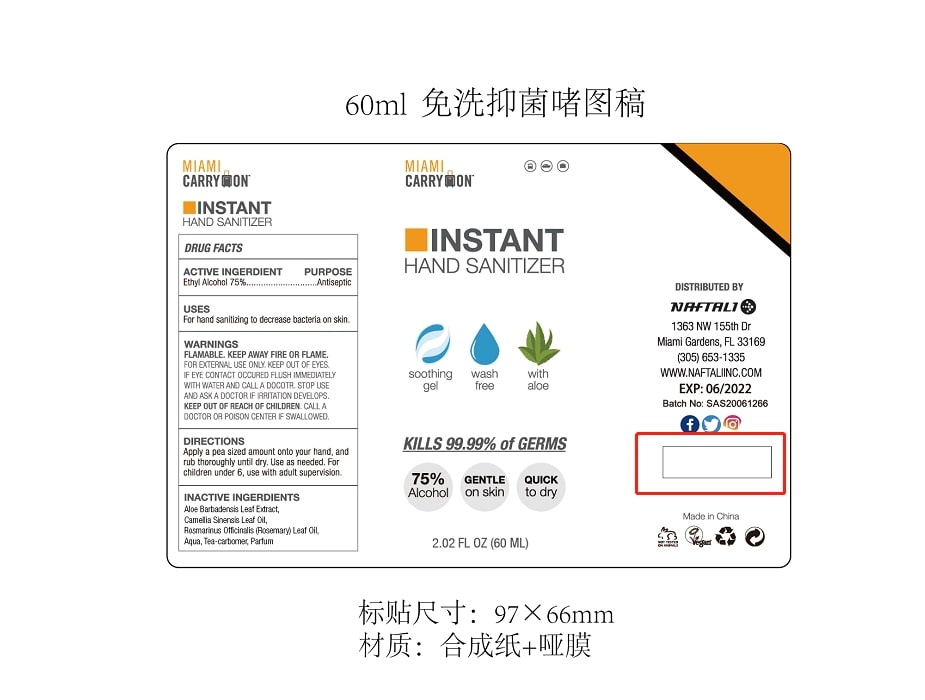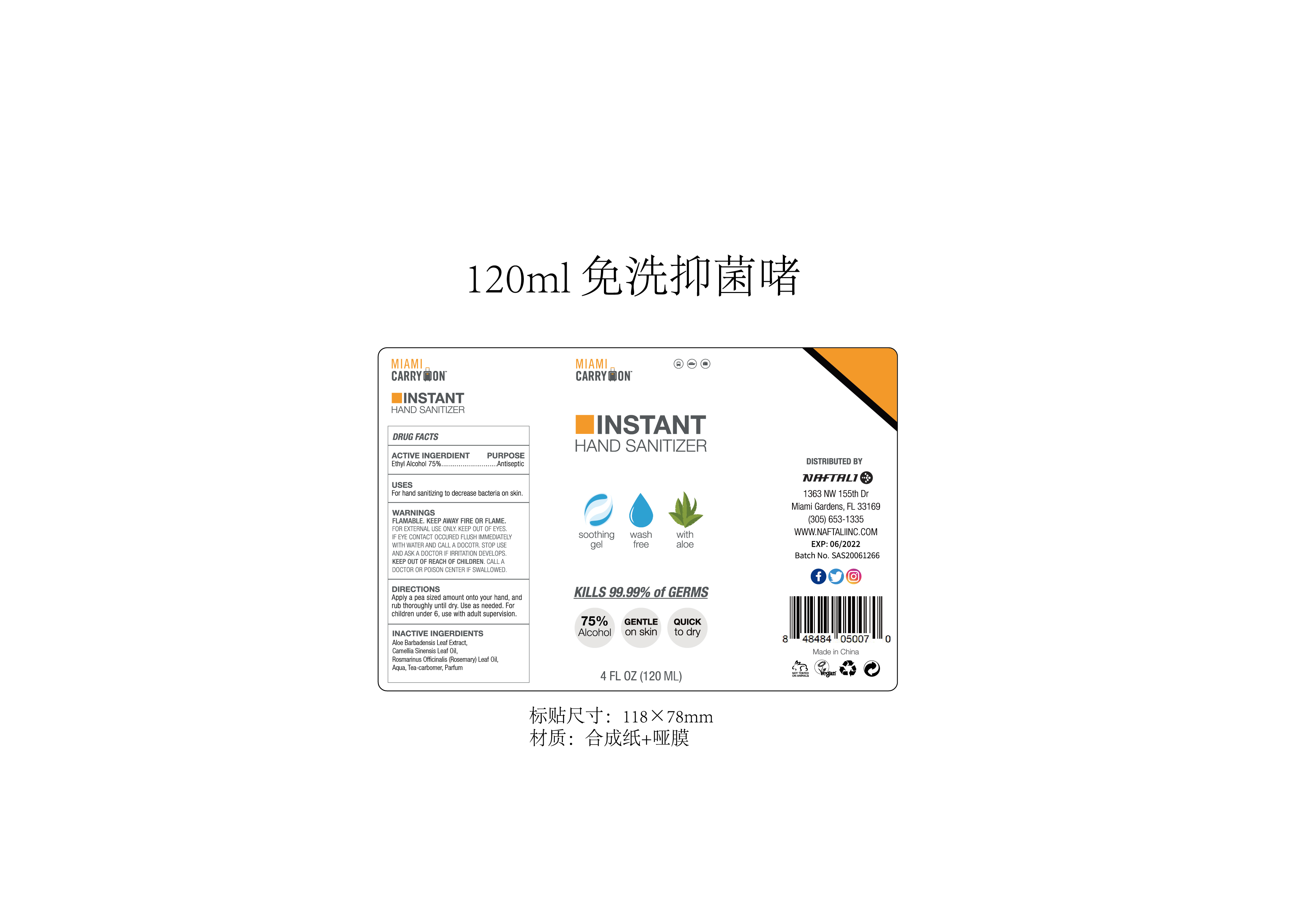 DRUG LABEL: INSTANT HAND SANITIZER
NDC: 74743-009 | Form: GEL
Manufacturer: Guangzhou Joy Claire Biological Technology Co., Ltd
Category: otc | Type: HUMAN OTC DRUG LABEL
Date: 20200630

ACTIVE INGREDIENTS: ALCOHOL 75 mL/100 mL
INACTIVE INGREDIENTS: TEA LEAF OIL; ALOE VERA LEAF; ROSEMARY OIL; WATER

INSTANT HAND SANITIZER

ACTIVE INGERDIENT

Ethyl Alcohol 75%

PURPOSE

Antiseptic

USES

Hand sanitizer to help reduce bacteria that potentially can cause disease. For use when soap and water are not available.

WARNINGS

For external use only. Flammable. Keep away from heat or flame.

DO NOT USE

• in children less than 2 months of age
• on ooen skin wounds

When using this product keep out of eyes, ears, and mouth. In case of contact with eyes, rinse eyes thoroughly with water.

Stop use and ask a doctor if irritation or rash occurs. These may be signs of a serious condition.

Keep out of reach of children. If swallowed, get medical help or contact Poison Control Center right away.

DIRECTIONS

• Place enough product on hands to cover all surfaces. Rub hands together until dry.
• Supervise children under 6 years of age when using this product to avoid swalloing.

Other information

• Store between 15-30C (59-86F)
• Avoid freezing and exessive heat aboce 40C (104F)

INACTIVE INGERDIENTS

Aloe Barbadensis Leaf Extract,Camellia Sinensis Leaf Oil.

Rosmarinus Officinalis(Rosemary) Leaf Oil, Aqua,Tea-carbomer, Parfum